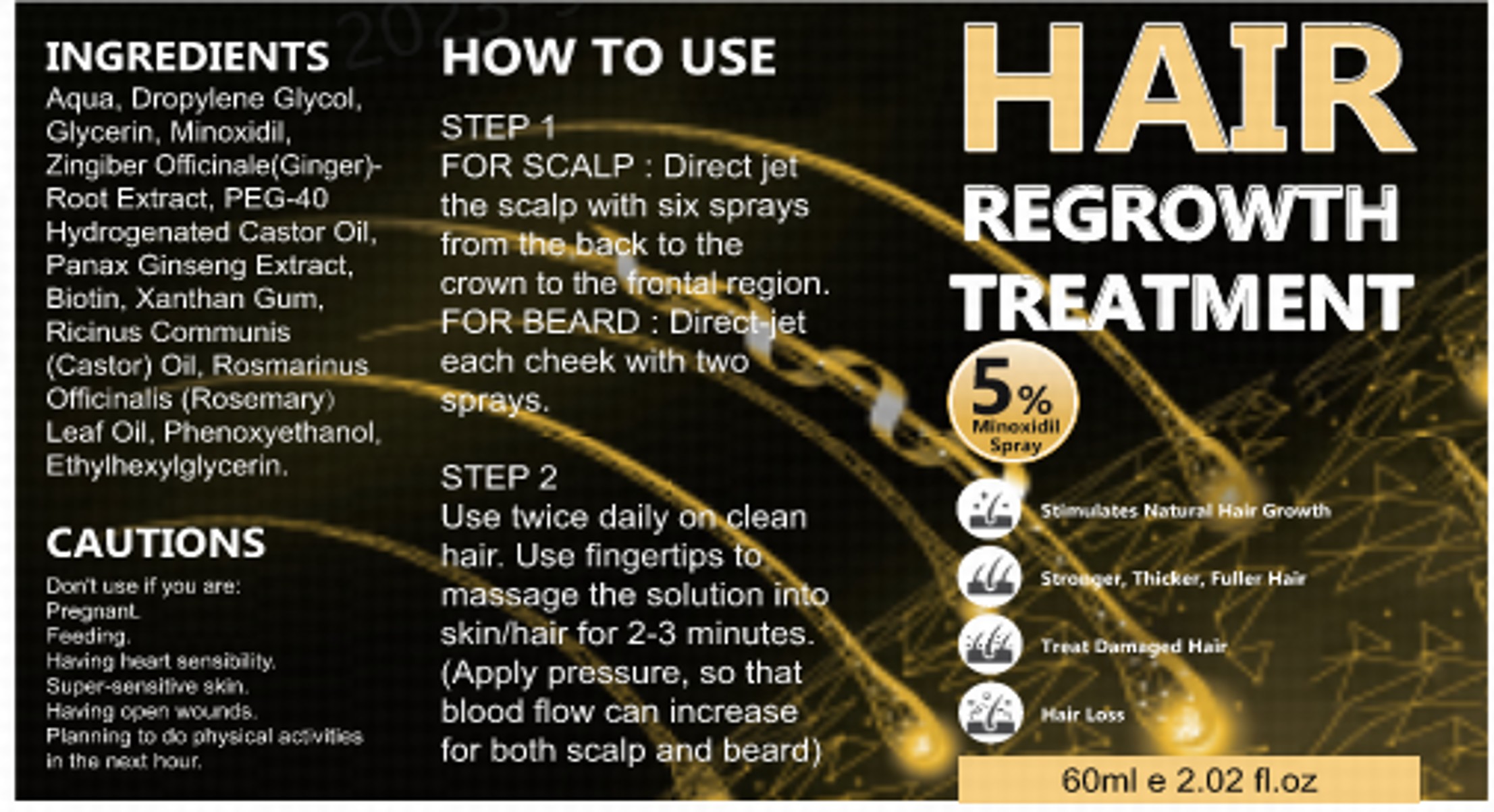 DRUG LABEL: Minoxidil HAIR Growth Sprays
NDC: 83788-401 | Form: LIQUID
Manufacturer: Xiamen Panmai Technology Co., Ltd
Category: otc | Type: HUMAN OTC DRUG LABEL
Date: 20250314

ACTIVE INGREDIENTS: MINOXIDIL 3 g/60 mL
INACTIVE INGREDIENTS: GLYCERIN; AQUA; PROPYLENE GLYCOL

Minoxidil Hair Growth Spray

ACTIVE INGREDIENT

Minoxidil 5%

PURPOSE

hair growth

KEEP OUT OF REACH OF CHILDREN SECTION

INDICATIONS AND USAGE

Stimulate hair growth.

WARNINGS

For external use only

DOSAGE AND ADMINISTRATION

FOR SCALP : Direct jetthe scalp with six spraysfrom the back to thecrown to the frontal region.FOR BEARD : Direct-jeteach cheek with twospray.
Use twice daily on cleanhair. Use fingertips tomassage the solution intoskin/hair for 2-3 minutes,(Apply pressure, so thatblood fow can increasefor both scalp and beard)

INACTIVE INGREDIENT

Aqua
Propylene Glycol
Glycerin